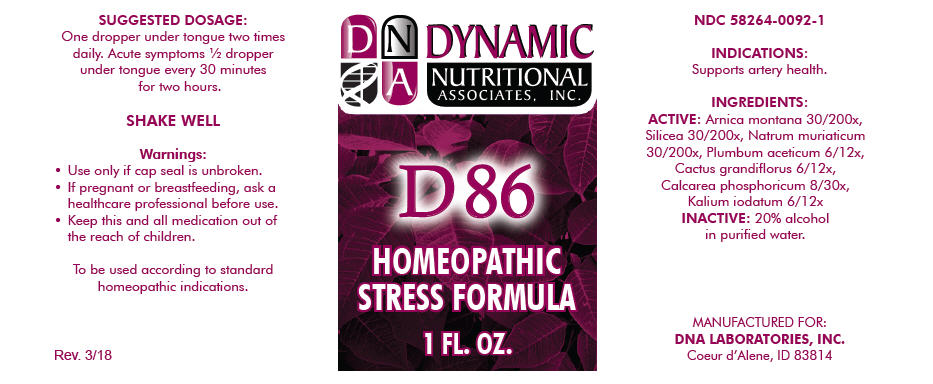 DRUG LABEL: D-86
NDC: 58264-0092 | Form: SOLUTION
Manufacturer: DNA Labs, Inc.
Category: homeopathic | Type: HUMAN OTC DRUG LABEL
Date: 20250113

ACTIVE INGREDIENTS: ARNICA MONTANA 30 [hp_X]/1 mL; SILICON DIOXIDE 30 [hp_X]/1 mL; SODIUM CHLORIDE 30 [hp_X]/1 mL; LEAD ACETATE ANHYDROUS 6 [hp_X]/1 mL; SELENICEREUS GRANDIFLORUS STEM 6 [hp_X]/1 mL; TRIBASIC CALCIUM PHOSPHATE 8 [hp_X]/1 mL; POTASSIUM IODIDE 6 [hp_X]/1 mL
INACTIVE INGREDIENTS: ALCOHOL; WATER

D-86

NDC 58264-0092-1

INDICATIONS

PURPOSE

Supports artery health.

INGREDIENTS

ACTIVE

Arnica montana 30/200x, Silicea 30/200x, Natrum muriaticum 30/200x, Plumbum aceticum 6/12x, Cactus grandiflorus 6/12x, Calcarea phosphoricum 8/30x, Kalium iodatum 6/12x

INACTIVE

20% alcohol in purified water.

SUGGESTED DOSAGE

One dropper under tongue two times daily. Acute symptoms ½ dropper under tongue every 30 minutes for two hours.

STORAGE AND HANDLING

SHAKE WELL

Warnings

- Use only if cap seal is unbroken.

PREGNANCY OR BREAST FEEDING

- If pregnant or breastfeeding, ask a healthcare professional before use.

KEEP OUT OF REACH OF CHILDREN

- Keep this and all medication out of the reach of children.

To be used according to standard homeopathic indications.

PRINCIPAL DISPLAY PANEL - 1 FL. OZ. Bottle Label

DYNAMIC
NUTRITIONAL
ASSOCIATES, INC.

D 86

HOMEOPATHIC
STRESS FORMULA

1 FL. OZ.